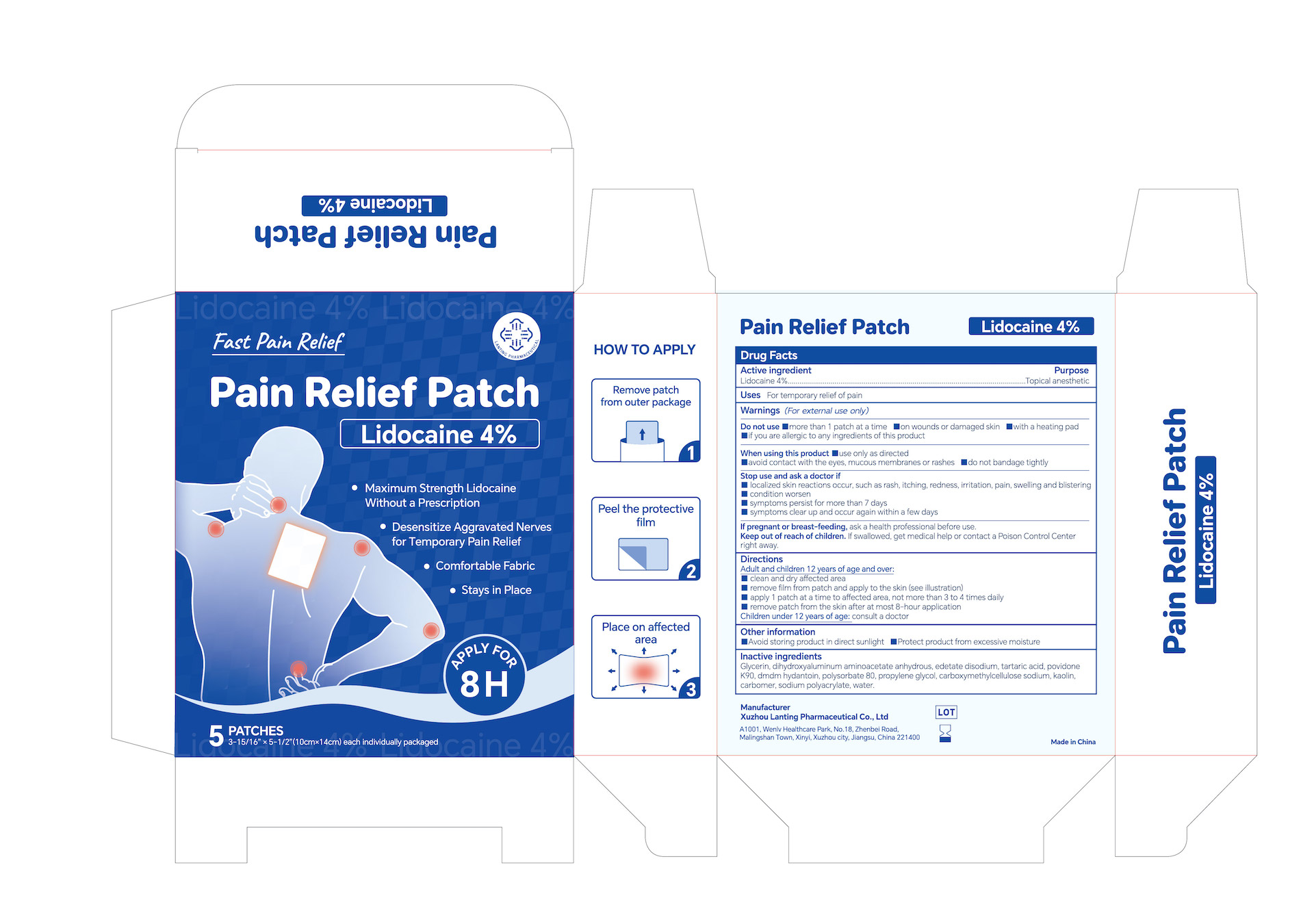 DRUG LABEL: 4% Lidocaine Pain Relief Patch
NDC: 85323-002 | Form: PATCH
Manufacturer: Xuzhou Lanting Pharmaceutical Co., Ltd
Category: otc | Type: HUMAN OTC DRUG LABEL
Date: 20250301

ACTIVE INGREDIENTS: LIDOCAINE HYDROCHLORIDE 4 g/100 g
INACTIVE INGREDIENTS: SODIUM POLYACRYLATE (2500000 MW); CARBOXYMETHYLCELLULOSE SODIUM; EDETATE DISODIUM; KAOLIN; DIHYDROXYALUMINUM AMINOACETATE ANHYDROUS; DMDM HYDANTOIN; CARBOMER; GLYCERIN; PROPYLENE GLYCOL; POVIDONE K90; POLYSORBATE 80; WATER; TARTARIC ACID

4% Lidocaine Pain Relief Patch, Package NDC Code: 85323-002-00

Active Ingredient

Active Ingredient: 4% Lidocaine

Purpose

Purpose: Topical anesthetic

Uses

Uses For temporary relief of minor aches & pains of muscles & joints associated with:

- simple backache
- arthritis
- strains
- bruises
- sprains

WARNINGS

Warnings (For external use only)

Do not use

- more than 1 patch at a time
- on wounds or damaged skin
- with a heating pad
- if you are allergic to any ingredients of this product

When using this product

- use only as directed
- aviod contact with the eyes, mucous membranes or rashes
- donot bandage tightly

Stop use and ask a doctor if

- localized skin reactions occur, such as reash, itching, redness, irritation, pain, swelling and blishtering
- condition worsen
- symptoms persist for more than 7 days
- symptoms clear up and occur again within a few days

If pregnant or breast-feeding, ask a health professional before use.

Keep out of reach of children. If swllowed, get medical help or contact a Poison Control Center right away.

Directions

Uses For temporary relief of minor aches & pains of muscles & joints associated with:

- simple backache
- arthritis
- strains
- bruises
- sprains

Adult and children 12 years of age and over:

clean and dry affected area
remove film from patch and apply to the skin (see illustration)
apply 1 patch at a time to affected area, not more than 3 to 4 times daily
remove patch from the skin after at most 8-hour application
Children under 12 years of age: consult a doctor

Other information

- Avoid storing product in direct sunlight
- Protect product from excessive moisture

Inactive ingredients

Glycerin, dihydroxyaluminum aminoacetate anhydrous, edetate disodium, tartaric acid, povidone K90, dmdm hydantoin, polysorbate 80, propylene glycol, carboxymethylcellulose sodium, kaolin, carbomer, sodium polyacrylate, water.

DOSAGE AND ADMINISTRATION

Adult and children 12 years of age and over:

clean and dry affected area
remove film from patch and apply to the skin (see illustration)
apply 1 patch at a time to affected area, not more than 3 to 4 times daily
remove patch from the skin after at most 8-hour application

Children under 12 years of age: consult a doctor

Keep out of reach of children. If swllowed, get medical help or contact a Poison Control Center right away.